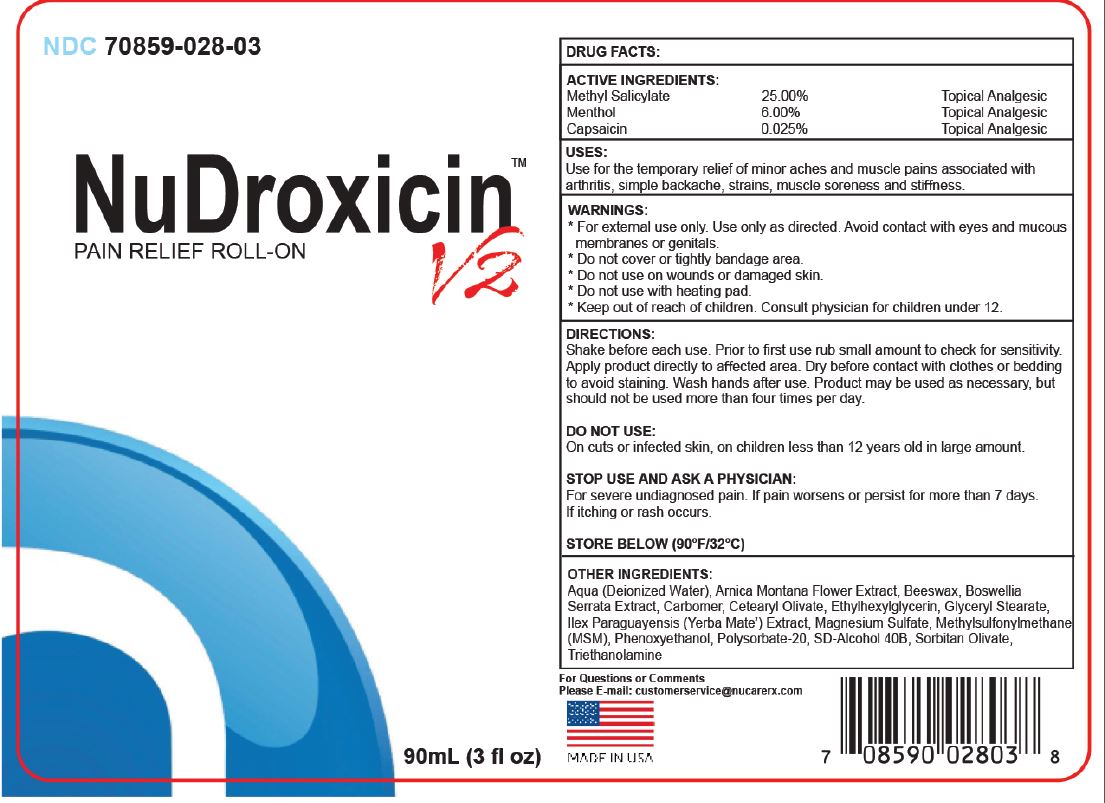 DRUG LABEL: NuDroxicin pain relief Roll-On
NDC: 70859-028 | Form: LIQUID
Manufacturer: NuCare Pharmaceuticals Inc
Category: otc | Type: HUMAN OTC DRUG LABEL
Date: 20180206

ACTIVE INGREDIENTS: METHYL SALICYLATE 250 mg/1 mL; MENTHOL 60 mg/1 mL; CAPSAICIN 0.25 mg/1 mL
INACTIVE INGREDIENTS: WATER; ARNICA MONTANA FLOWER; YELLOW WAX; INDIAN FRANKINCENSE; CARBOXYPOLYMETHYLENE; CETEARYL OLIVATE; ETHYLHEXYLGLYCERIN; GLYCERYL MONOSTEARATE; ILEX PARAGUARIENSIS LEAF; MAGNESIUM SULFATE, UNSPECIFIED FORM; DIMETHYL SULFONE; PHENOXYETHANOL; POLYSORBATE 20; SORBITAN OLIVATE

NuDroxicin pain relief Roll-On

ACTIVE INGREDIENTS:

Methyl Salicylate 25.00%
Menthol 6.00%
Capsaicin 0.025%

PURPOSE

Topical Analgesic

USES:

Use for the temporary relief of minor aches and muscle pains associated with arthritis, simple backache, strains, muscle soreness and stiffness.

WARNINGS:

- For external use only. Use only as directed. Avoid contact with eyes and mucous membranes or genitals.
- Do not cover or tightly bandage area.
- on wounds or damaged skin.
- Do not use with heating pad.

Do not use

On cuts or infected skin, on children less than 12 years old in large amount.

STOP USE AND ASK A PHYSICIAN:

For severe undiagnosed pain. If pain worsens or persist for more than 7 days. If itching or rash occurs.

Keep out of reach of children.

Consult physician for children under 12.

DIRECTIONS:

Shake before each use. Prior to first use rub small amount to check for sensitivity. Apply product directly to affected area. Dry before contact with clothes or bedding to avoid staining. Wash hands after use. Product may be used as necessary, but should not be used more than four times per day.

STORE BELOW (90°F/32°C)

OTHER INGREDIENTS:

Aqua (Deionized Water), Arnica Montana Flower Extract, Beeswax, Boswellia Serrata Extract, Carbomer, Cetearyl Olivate, Ethylhexylglycerin, Glyceryl Stearate, Ilex Paraguayensis (Yerba Mate’) Extract, Magnesium Sulfate, Methylsulfonylmethane (MSM), Phenoxyethanol, Polysorbate-20, SD-Alcohol 40B, Sorbitan Olivate, Triethanolamine